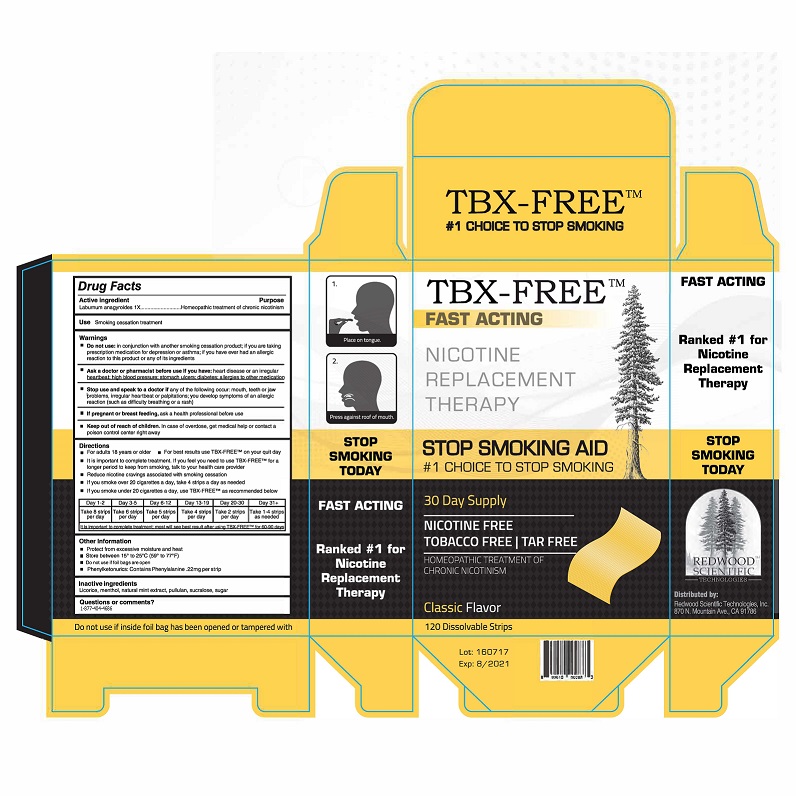 DRUG LABEL: TBX-Free
NDC: 69305-002 | Form: STRIP
Manufacturer: Advanced Men’s Institute LLC
Category: homeopathic | Type: HUMAN OTC DRUG LABEL
Date: 20180112

ACTIVE INGREDIENTS: LABURNUM ANAGYROIDES FLOWERING TOP 1 [hp_X]/10 [hp_X]
INACTIVE INGREDIENTS: MINTLACTONE; SUCROSE; LICORICE; PULLULAN; MENTHOL, UNSPECIFIED FORM; SUCRALOSE

TBX-Free

PURPOSE

Homeopathic treatment of chronic nicotinism

KEEP OUT OF REACH OF CHILDREN

Incase of overdose, get medical help or contact your poison control center right away

Use

Smoking cessation treatment

DIRECTIONS
•Adults 18 years or older
•Begin using TBX-Free on your quit day
•It is important to complete treatment. If you feel you need to use TBX-Free for a longer period to keep from smoking, talk to your health care provider.

- Reduce nicotine cravings associated with smoking cessation
- If you smoke over 20 cigarettes a day, take 4 strips a day as needed
- If you smoke under 20 cigarettes a day, use TBX-FREE as recommended below:
  -
    Day 1-2 | Day 3-5 | Day 6-12 | Day 13-19 | Day 20-30 | Day 31 +
    Take 8 strips per day | Take 6 strips per day | Take 5 strips per day | Take 4 strips per day | Take 2 stips per day | Take 1-4 strips per day as needed
    It is important to complete treatment: most will see best result after using TBX-FREE for 60-90 days

WARNING

- Do not use: in conjunction with another smoking cessation product; if you are taking prescription medication for depression or asthma; if you have ever had an allergic reaction to this product or any of its ingredients.
- Ask a doctor or pharmacist before use if you have: heart disease or an irregular heartbeat; high blood pressure; stomach ulcers; diabetes; allergies to other medication
- Stop use and speak to a doctor if any of the following occur: mouth, teeth, or jaw problems, irregular heartbeat or palpitations; you develop symptoms of an allergic reaction (such as difficulty breathing or a rash)
- If pregnant or breast feeing, ask a health professional before use
- Keep out of reach of children. In case of overdose, get medical help or contact a poison control center right away.

INACTIVE INGREDIENTS

Pullulan, Natural mint extract, Sugar, Menthol, Licorice, Sucralose

OTHER INFORMATION
•protect from excessive moisture and heat
•store between 15° to 25° C (59° to 77° F)

- Do not use if tamper-evident seal is broken
- Phenylketonurics: Contains Phenylalanine .22 mg Per Strip

QUESTIONS OR COMMENTS?

1-800-404-4686

ACTIVE INGREDIENT

Laburnum anagyroides 1X